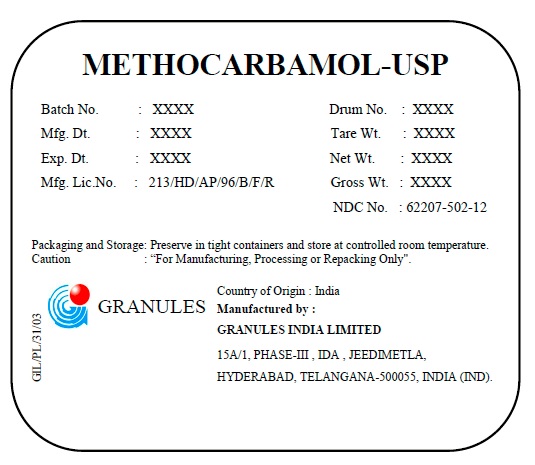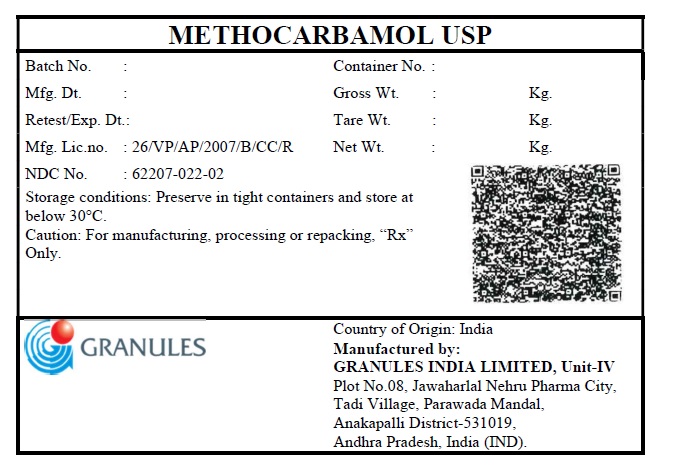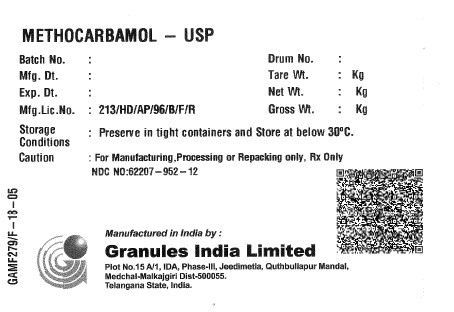 DRUG LABEL: Methocarbamol
NDC: 62207-502 | Form: POWDER
Manufacturer: Granules India Limited
Category: other | Type: BULK INGREDIENT
Date: 20251024

ACTIVE INGREDIENTS: METHOCARBAMOL 1 kg/1 kg

METHOCARBAMOL – USP

DESCRIPTION

METHOCARBAMOL-USP

Batch No.: XXXX | Drum No.:XXXX
Mfg.Dt.: XXXX | Tare Wt.: XXXX
Exp.Dt.: XXXX | Net Wt.: XXXX
Mfg. Lic. No.: 213/HD/AP/96/B/F/R | Gross Wt.: XXXX; NDC No. : 62207-952-12

Packaging and Storage: Preserve in tight containers and store at below 30ºC.
Caution : “For Manufacturing, Processing or Repacking Only".

HOW SUPPLIED

GIL/PL/31/03

Country of Origin: India

Manufactured by:
Granules India Limited
Plot No.: 15A/1,
IDA, Phase –III,
Jeedimetla, Quthbullapur Mandal,
Medchal-Malkajgiri District-500 055
Telangana State, India